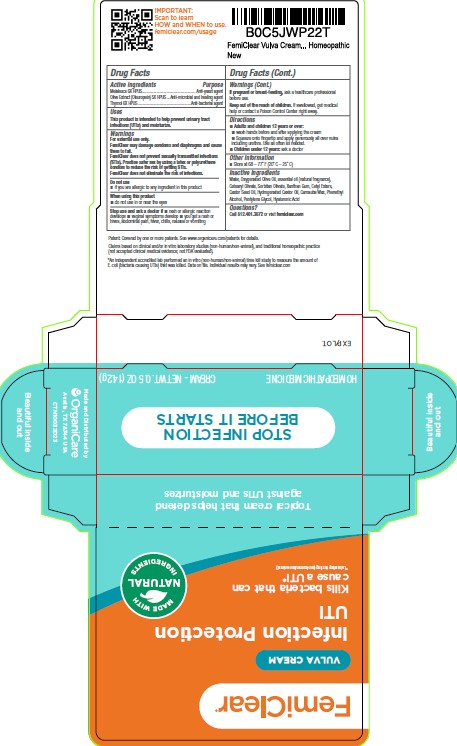 DRUG LABEL: FemiClear Vulva Cream
NDC: 71042-027 | Form: CREAM
Manufacturer: OrganiCare Nature's Science, LLC
Category: homeopathic | Type: HUMAN OTC DRUG LABEL
Date: 20251020

ACTIVE INGREDIENTS: THYMOL 0.0001 kg/100 kg; MELALEUCA CAJUPUTI LEAF OIL 0.0001 kg/100 kg
INACTIVE INGREDIENTS: PHENYLETHYL ALCOHOL 1 kg/100 kg; HYALURONATE SODIUM 0.5 kg/100 kg; XANTHAN GUM 0.2 kg/100 kg; PENTYLENE GLYCOL 2 kg/100 kg; CETYL ESTERS WAX 6 kg/100 kg

FemiClear Vulva Cream

WARNINGS

For external use only.

FemiClear may damage condoms and diaphragms and cause them to fail.

FemiClear does not prevent sexually transmitted infections (STIs). Practice safer sex by using latex or polyurethane condom to reduce the risk of getting STIs.

FemiClear does not eliminate the risk of infections.

DO NOT USE

 if you are allergic to any ingredient in this product

 do not use in or near the eyes

Stop use and ask a doctor if  rash or allergic reaction
develops  vaginal symptoms develop  you get a rash or
hives, abdominal pain, fever, chills, nausea or vomiting

PREGNANCY OR BREAST FEEDING

If pregnant or breast-feeding, ask a healthcare professional
before use.

KEEP OUT OF REACH OF CHILDREN

Keep out of the reach of children. If swallowed, get medical
help or contact a Poison Control Center right away.

ACTIVE INGREDIENT

Melaleuca 6X HPUS................................................ Anti-yeast agent
Olive Extract (Oleuropein) 5X HPUS ...Anti-microbial and healing agent
Thymol 6X HPUS................................................Anti-bacterial agent

INACTIVE INGREDIENT

Water, Oxygenated Olive Oil, essential oil (natural fragrance),
Cetearyl Olivate, Sorbitan Olivate, Xanthan Gum, Cetyl Esters,
Castor Seed Oil, Hydrogenated Castor Oil, Carnauba Wax, Phenethyl
Alcohol, Pentylene Glycol, Hyaluronic Acid

Questions?
Call 512.401.3572 or visit femiclear.com

DOSAGE AND ADMINISTRATION

Squeeze onto fingertip and apply generously all over vulva including urethra. Ues as often as needed.

INDICATIONS AND USAGE

Use as often as needed.

PURPOSE

This product is intended to help prevent urinary tract infections (UTIs) and moisturize.